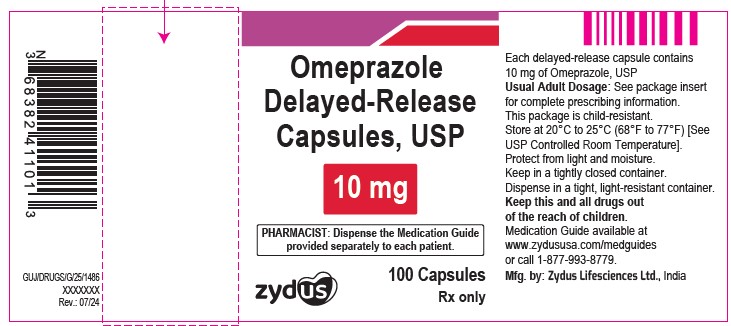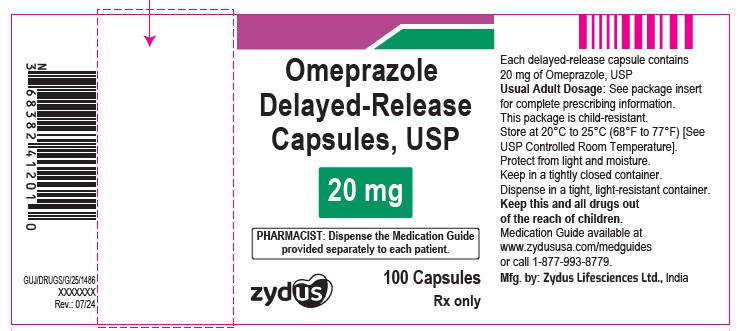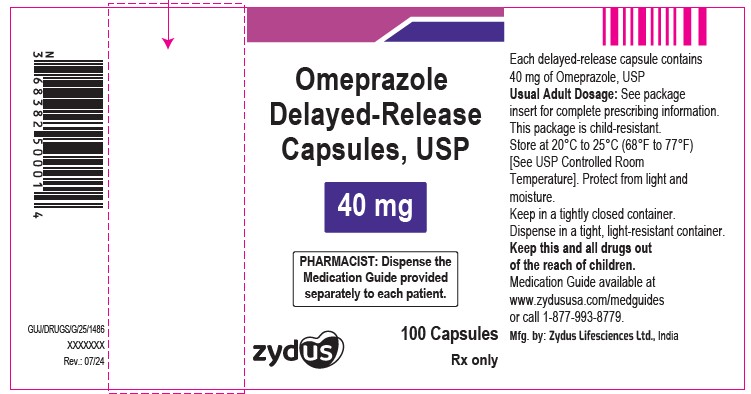 DRUG LABEL: Omeprazole
NDC: 65841-759 | Form: CAPSULE, DELAYED RELEASE
Manufacturer: Zydus Lifesciences Limited
Category: prescription | Type: HUMAN PRESCRIPTION DRUG LABEL
Date: 20241203

ACTIVE INGREDIENTS: OMEPRAZOLE 10 mg/1 1
INACTIVE INGREDIENTS: ACETONE; FD&C BLUE NO. 1; FD&C GREEN NO. 3; FD&C RED NO. 3; FERROSOFERRIC OXIDE; GELATIN; HYDROXYPROPYL CELLULOSE (1600000 WAMW); HYPROMELLOSE PHTHALATE (31% PHTHALATE, 170 CST); HYPROMELLOSES; POLYETHYLENE GLYCOL, UNSPECIFIED; POTASSIUM HYDROXIDE; PROPYLENE GLYCOL; SHELLAC; SODIUM LAURYL SULFATE; SODIUM PHOSPHATE, DIBASIC, DIHYDRATE; SUCROSE; TALC; TITANIUM DIOXIDE; TRIETHYL CITRATE

OMEPRAZOLE DELAYED-RELEASE CAPSULES, USP

PACKAGE LABEL.PRINCIPAL DISPLAY PANEL

NDC 65841-759-01 in bottle of 100 Capsules

Omeprazole Delayed-release Capsules USP, 10 mg

Rx only

100 Capsules

NDC 65841-760-01 in bottle of 100 Capsules

Omeprazole Delayed-release Capsules USP, 20 mg

Rx only

100 Capsules

NDC 65841-761-01 in bottle of 100 Capsules

Omeprazole Delayed-release Capsules USP, 40 mg

Rx only

100 Capsules